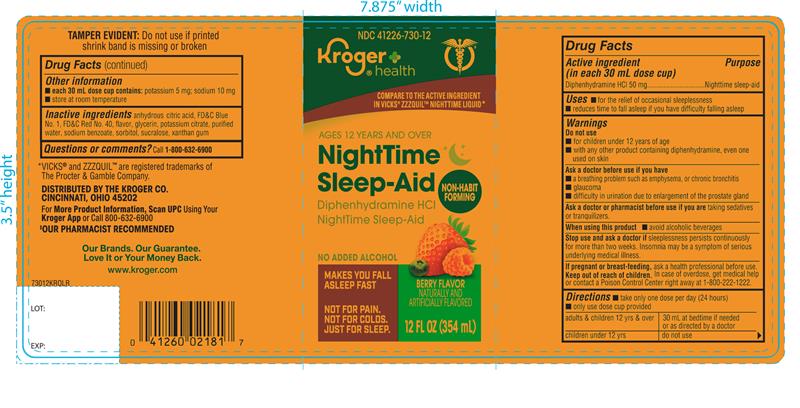 DRUG LABEL: KROGER Nighttime Sleep-Aid
NDC: 41226-730 | Form: LIQUID
Manufacturer: KROGER COMPANY
Category: otc | Type: HUMAN OTC DRUG LABEL
Date: 20250812

ACTIVE INGREDIENTS: DIPHENHYDRAMINE HYDROCHLORIDE 50 mg/30 mL
INACTIVE INGREDIENTS: ANHYDROUS CITRIC ACID; FD&C BLUE NO. 1; FD&C RED NO. 40; GLYCERIN; POTASSIUM CITRATE; WATER; SODIUM BENZOATE; SORBITOL; SUCRALOSE; XANTHAN GUM

KROGER Nighttime Sleep-Aid 12 FL OZ

Drug Facts

Active ingredient (in each 30 mL dose cup)

Diphenhydramine HCl 50 mg

Purpose

Nighttime sleep-aid

Uses

- for the relief of occasional sleeplessness
- reduces time to fall asleep if you have difficulty falling asleep

Warnings

Do not use

- for children under 12 years of age
- with any other product containing diphenhydramine, even one used on skin

Ask a doctor before use if you have

- a breathing problem such as asthma, emphysema, or chronic bronchitis
- glaucoma
- difficulty in urination due to enlargement of the prostate gland

Ask a doctor or pharmacist before use if you aretaking sedatives or tranquilizers.

When using this product

- avoid alcoholic beverages

Stop use and ask a doctor ifsleeplessness persists continuously for more than two weeks. Insomnia may be a symptom of serious underlying medical illness.

PREGNANCY OR BREAST FEEDING

If pregnant or breast-feeding, ask a health professional before use.

Keep out of reach of children.

Overdose warning:

Taking more than directed can cause serious health problems. In case of overdose, get medical help or contact a Poison Control Center right away.1-800-222-1222

Directions

- take only one dose per day (24 hours)
- Only use dose cup provided

adults & children 12 yrs & over | 30 mL at bed time if needed or as directed by a doctor
Children under 12 yrs | Do not use

Other information

- each 30 mL dose cup contains: potassium 5 mg; sodium 10 mg
- store at room temperature

Inactive ingredients

anhydrous citric acid, FD&C blue 1, FD&C red 40, flavor, glycerin, potassium citrate, purified water, sodium benzoate, sorbitol, sucralose, xanthan gum.

Questions or comments?

1-866-467-2748

PRINCIPAL DISPLAY PANEL

Compare to the active ingredient in ZzzQuil™ Nighttime Sleep-Aid*

NDC 41226-730-12

Nighttime

Sleep-Aid

Diphenhydramine HCl

- Non-habit forming
- Makes you fall asleep fast

Berry Flavor

Naturally & artificially flavored

No added alcohol

Not for pain. Not for Colds.

Just for Sleep

12 FL. OZ. (354 mL)

TAMPER EVIDENT:Do not use if printed shrink band is missing or broken

*This product is not manufactured or distributed by Proctor & Gamble, the distributor of ZzzQuil™ Nighttime Sleep-Aid.

Distributed by: